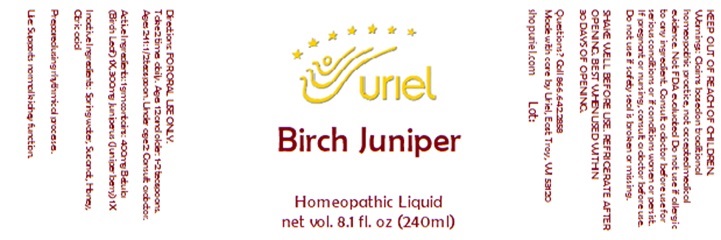 DRUG LABEL: Birch Juniper
NDC: 48951-2149 | Form: LIQUID
Manufacturer: Uriel Pharmacy Inc
Category: homeopathic | Type: HUMAN OTC DRUG LABEL
Date: 20251118

ACTIVE INGREDIENTS: JUNIPER BERRY 1 [hp_X]/1 mL; BETULA PENDULA BARK 1 [hp_X]/1 mL
INACTIVE INGREDIENTS: WATER; HONEY; SUCROSE; CITRIC ACID MONOHYDRATE

Birch Juniper

INDICATIONS AND USAGE

Directions: FOR ORAL USE ONLY.

DOSAGE AND ADMINISTRATION

Take 2 times daily. Ages 12 and older: 1-2 teaspoons. Ages 2-11: 1/2 teaspoon. Under age 2: Consult a doctor.

ACTIVE INGREDIENT

Active Ingredients: 1gm contains: 400mg Betula (Birch Leaf) 1X, 300mg Juniperus (Juniper berry) 1X

Inactive Ingredients: Spring water, Sucanat, Honey, Citric acid

Prepared using rhythmical processes.

PURPOSE

Use: Supports normal kidney function.

WARNINGS

Warnings: Claims based on traditional homeopathic practice, not accepted medical evidence. Not FDA evaluated Do not use if allergic to any ingredient. Consult a doctor before use for serious conditions or if conditions worsen or persist. If pregnant or nursing, consult a doctor before use. Do not use if safety seal is broken or missing.

SHAKE WELL BEFORE USE. REFRIGERATE AFTER OPENING. BEST WHEN USED WITHIN
30 DAYS OF OPENING.

KEEP OUT OF REACH OF CHILDREN.

Questions? Call 866.642.2858
Made with care by Uriel, East Troy, WI 53120
shopuriel.com Lot: